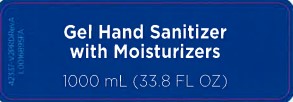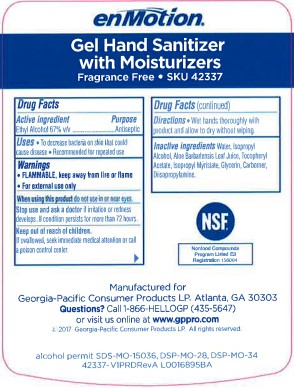 DRUG LABEL: Ethyl Alcohol
NDC: 54622-015 | Form: SOLUTION
Manufacturer: Georgia-Pacific Consumer Products LP 
Category: otc | Type: HUMAN OTC DRUG LABEL
Date: 20260204

ACTIVE INGREDIENTS: ALCOHOL 0.67 mL/1 mL
INACTIVE INGREDIENTS: WATER; ISOPROPYL ALCOHOL; ALOE VERA LEAF; TOCOPHEROL; ISOPROPYL MYRISTATE; GLYCERIN; CARBOMER 1342; DIISOPROPYLAMINE

enMotion 015.000/015AA-AB
Gel Hand Sanitizer with Moisturizers Fragrance Free SKU 42337

Active ingredient

Ethyl Alcohol 67% v/v

Purpose

Antiseptic

Uses

- To decrease bacteria on skin that could cause disease
- Recommended for repeated use

Warnings

- FLAMMABLE, keep away from fire or flame
- For external use only

When using this product

do not use in or near eyes.

Stop use and ask a doctor if

irritation or redness develops. If condition persists for more than 72 hours consult a doctor.

Keep out of reach of children.

If swallowed, seek immediate medical attention or call a poison control center.

Directions

Wet hands thoroughly with product and allow to dry without wiping.

Inactive ingredients

water, isopropyl alcohol, Aloe barbadensis leaf juice, tocopheryl acetate, isopropyl myristate, glycerin, carbomer, diisopropylamine

ADVERSE REACTION

NSF

Nonfood Compounds

Program Listed E3

Registration 158094

Manufactured for Georgia-Pacific Consumer Products LP. Atlanta, GA 30303

Quesitons? Call 1-866-HELLOGP (435-5647) or visit us online at www.gppro.com

(c) 2017 Georgia Pacific Consumer Products LP. All rights reserved.

alcohol permit SDS-MO-15036, DSP-MO-28, DSP-MO-34

42336-7-V1PRDRevA L0016895BA

principal display panel

Gel Hand Sanitizer with Moisturizers

1000 mL (33.8 FL OZ)